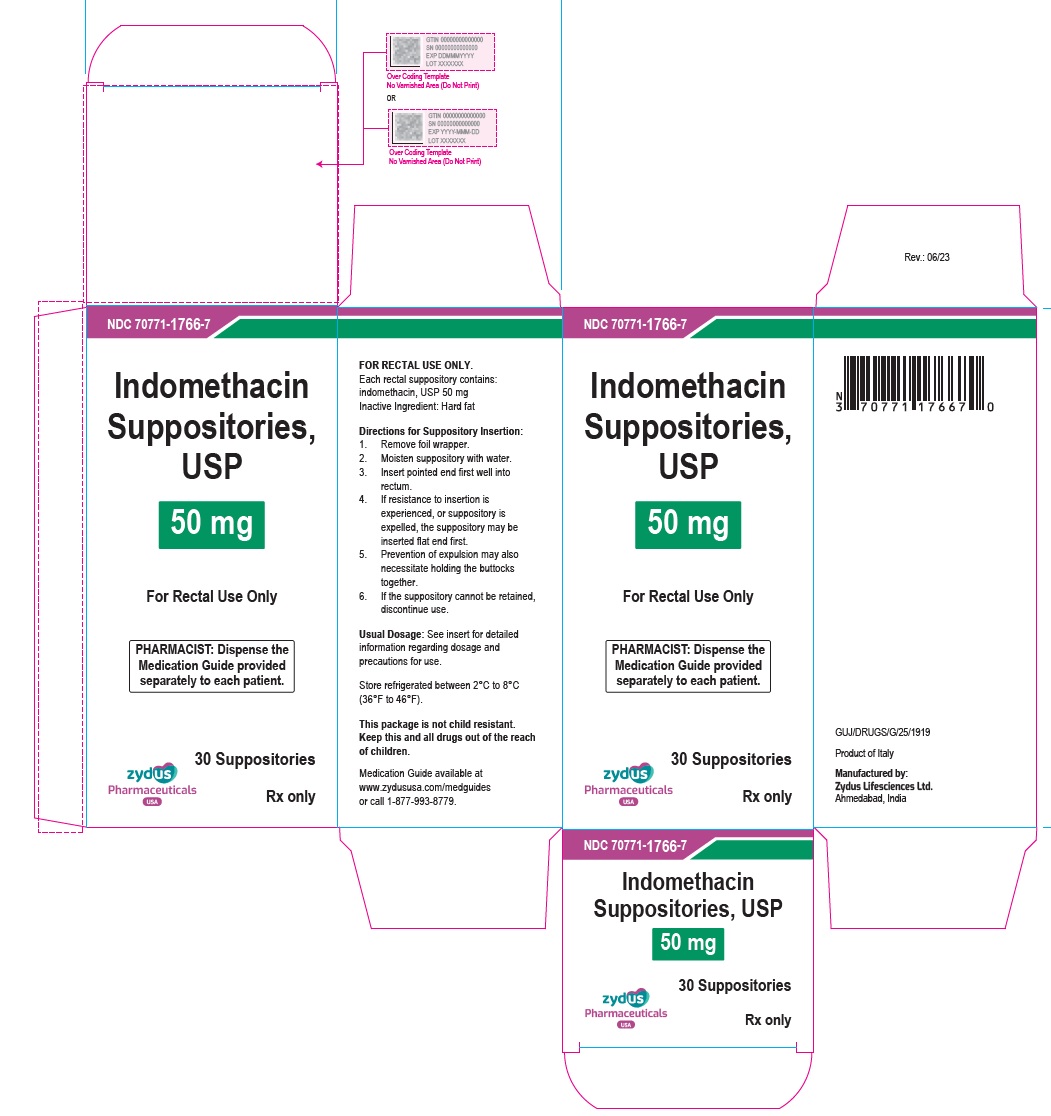 DRUG LABEL: Indomethacin
NDC: 70771-1766 | Form: SUPPOSITORY
Manufacturer: Zydus Lifesciences Limited
Category: prescription | Type: HUMAN PRESCRIPTION DRUG LABEL
Date: 20230803

ACTIVE INGREDIENTS: INDOMETHACIN 50 mg/1 1
INACTIVE INGREDIENTS: HARD FAT

INDOMETHACIN suppositories, for rectal use

PACKAGE LABEL.PRINCIPAL DISPLAY PANEL

NDC 70771-1766-7

Indomethacin Suppositories USP, 50 mg

30 rectal suppositories

Rx only